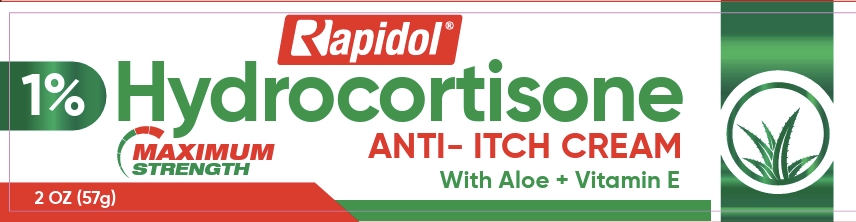 DRUG LABEL: Rapidol
NDC: 55758-420 | Form: CREAM
Manufacturer: Pharmadel LLC
Category: otc | Type: HUMAN OTC DRUG LABEL
Date: 20260123

ACTIVE INGREDIENTS: HYDROCORTISONE 1 g/100 g
INACTIVE INGREDIENTS: ALOE VERA LEAF; CETOSTEARYL ALCOHOL; EDETATE DISODIUM; GLYCERYL MONOSTEARATE; MINERAL OIL; WATER; .ALPHA.-TOCOPHEROL ACETATE; CHLOROCRESOL; SODIUM METABISULFITE; CETEARETH-20; PROPYLENE GLYCOL

Rapidol Hydrocortisone 1%(DIL)

Active ingredient & Purpose

Active ingredient | Purpose
Hydrocortisone 1%............................................... | Anti-itch

Uses

For the temporary relief of itching associated with minor skin irritations, inflammation, and rashes due to

- eczema
- insect bites
- poison ivy
- poison oak
- poison sumac
- soaps
- detergent
- cosmetics
- jewelry
- seborrheic dermatitis
- psoriasis
- and for external feminine, genital, and anal itching
- for other uses of this product should only be under the advice and supervision of a doctor

Warnings

FOR EXTERNAL USE ONLY. Avoid contact with the eyes.

Do not use

- for treatment of diaper rash. Consult a doctor
- if you have a vaginal discharge. Consult a doctor.
- with any other hydrocortisone product unless you have consulted a doctor

When using this product

- for external anal itching: Do not exceed the recommended daily dosage unless directed by a doctor. In case of bleeding, consult a doctor promptly. Do not put this product into the rectum by using fingers or any mechanical device or applicator.

Stop use and ask a doctor if

- condition worsens
- symptoms persist for more than 7 days and occur again within a few days

If pregnant or breastfeeding,

ask a doctor before use.

KEEP OUT OF REACH OF CHILDREN

If accidental ingestion, seek medical help or contact a Poison Control Center immediately.

Directions

For itchy skin, irritations, inflammation, rashes and external feminine and genital itching:

- adults and children 2 years of age and older: apply to the affected area not more than 3 to 4 times daily.
- children under 2 years of age: do not use, consult a doctor

For external anal itching:

- adults: when practical, cleanse the affected area with mild soap and warm water and rinse thoroughly. Gently dry by

patting or blotting with toilet tissue or a soft cloth before application of this product.

- children under 12 years of age: consult a doctor

Other information

- store in a cool dry place
- do not use if foil seal under cap is torn, broken, or missing

Inactive ingredients

Aloe vera, ceteareth-20, cetostearyl alcohol, chlorocresol, edetate disodium, glyceryl monostearate, mineral oil, propylene glycol, sodium metabisulfite, tocopherol acetate (vitamin E), water

Questions?

+1-866-359-3478 (M-F) 9AM to 5 PM EST or www.pharmadel.com

Dist. by/ por

Pharmadel LLC

New Castle, DE 19720 • www.pharmadel.com

+1-866-359-3478

Made in India / Hecho en India

†This product is not manufactured or distributed by Chattem, Inc. a division of Sanofi owner of the Cortizone-10® trademark.